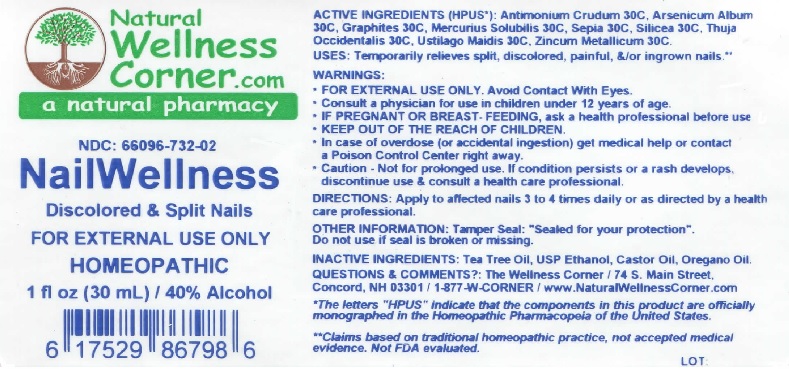 DRUG LABEL: NailWellness
NDC: 66096-732 | Form: LIQUID
Manufacturer: OHM PHARMA INC.
Category: homeopathic | Type: HUMAN OTC DRUG LABEL
Date: 20180129

ACTIVE INGREDIENTS: ANTIMONY TRISULFIDE 30 [hp_C]/30 mL; ARSENIC TRIOXIDE 30 [hp_C]/30 mL; GRAPHITE 30 [hp_C]/30 mL; MERCURIUS SOLUBILIS 30 [hp_C]/30 mL; SEPIA OFFICINALIS JUICE 30 [hp_C]/30 mL; SILICON DIOXIDE 30 [hp_C]/30 mL; THUJA OCCIDENTALIS LEAFY TWIG 30 [hp_C]/30 mL; USTILAGO MAYDIS 30 [hp_C]/30 mL; ZINC 30 [hp_C]/30 mL
INACTIVE INGREDIENTS: TEA TREE OIL; ALCOHOL; CASTOR OIL; OREGANO LEAF OIL

NailWellness

ACTIVE INGREDIENT

ACTIVE INGRDIENTS (HPUS*): Antimoniyum Crudum 30C, Arsenicum Album 30C, Graphites 30C, Mercurius Solubilis 30C, Sepia 30C, Silicea 30C, Thuja Occidentalis 30C, Ustilago Maidis 30C, Zincum Metallicum 30C.

INDICATIONS AND USAGE

USES: Temporarily relieves split, discolored, painful, &/or ingrown nails. **

WARNINGS:

• FOR EXTERNAL USE ONLY. Avoid Contact with Eyes

• Consult a physician for use in children under 12 kyears of age.

• IF PREGNANT OR BREASE - FEEDING, ask a health professional before use

• KEEP OUT OF THE REACH OF CHILDREN

• In case of overdose (or accidental ingestion) get medical help or contact a Poison Control Center right away.

• Caution - Not for prolonged use. If condition persists or a rash develops, discontinue use & consult a health care professional.

KEEP OUT OF THE REACH OF CHILDREN

DOSAGE AND ADMINISTRATION

DIRECTIONS: Apply to affected nsils 3 to 4 times daily or as directed by a health care professional.

OTHER INFORMATION: Tamper Seal: "Sealed for your protection".

Do not use of seal is broken or missing.

*The letters "HPUS" Indicate that the componenets in this product are officially monographed in the Homeopathic

Pharmacopeia of the Unitwed States.

**Claims based on traditional homeopathic practice, not accepted medical evidence. Not FDA evaluated.

INACTIVE INGREDIENT

INACTIVE INGREDIENTS: Tee Tree Oil, USP Ethanol, Castor Oil, Oregano Oil.

QUESTIONS

QUESTIONS & COMMENTS?: The Wellness Corner / 74 S. Main Street.

Concord, NH 03301 / 1-877-W-CORNER / www.NaturalWellnessCorner.com

PACKAGE LABEL

Natural Wellness Corner.com

a natural pharmacy

NDC: 66096-732-02

NailWellness

Discolored & Split Nails

FOR EXTGERNAL USE ONLY

HOMEOPATHIC

1 fl oz (30mL) / 40% Alcohol

PURPOSE

Temporarily relieves split, discolored, painful, &/ or infrown nails.